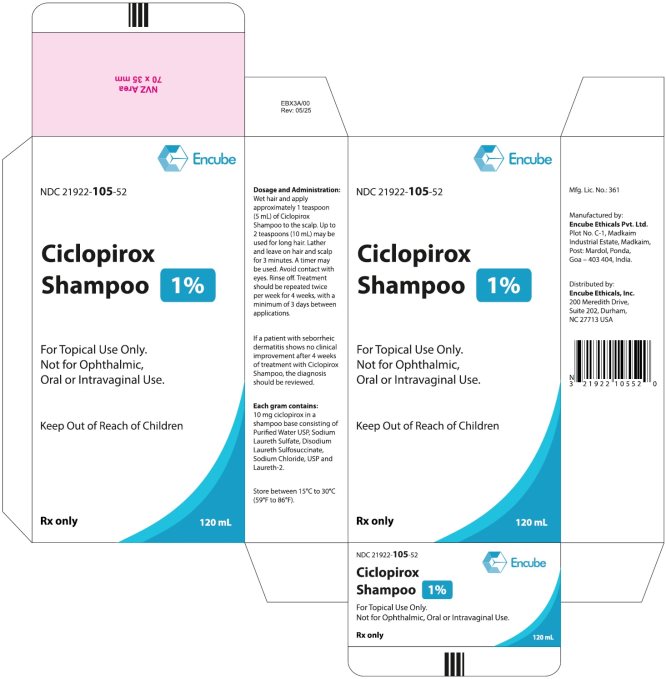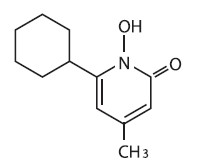 DRUG LABEL: CICLOPIROX
NDC: 21922-105 | Form: SHAMPOO
Manufacturer: Encube Ethicals, Inc.
Category: prescription | Type: HUMAN PRESCRIPTION DRUG LABEL
Date: 20260130

ACTIVE INGREDIENTS: CICLOPIROX 1 g/100 mL
INACTIVE INGREDIENTS: SODIUM LAURETH-2 SULFATE; DISODIUM LAURETH SULFOSUCCINATE; SODIUM CHLORIDE; LAURETH-2; WATER

HIGHLIGHTS OF PRESCRIBING INFORMATION

These highlights do not include all the information needed to use Ciclopirox Shampoo safely and effectively. See full prescribing information for CICLOPIROX SHAMPOO.
Ciclopirox Shampoo 1% For topical use
Initial U.S. Approval: 1982

1 INDICATIONS AND USAGE

- Ciclopirox shampoo is an antifungal indicated for the topical treatment of seborrheic dermatitis of the scalp in adults. (1)

2 DOSAGE AND ADMINISTRATION

- Apply approximately 1 teaspoon of ciciopirox shampoo to the scalp twice per week for 4 weeks. (2)
- For topical use only. Not for ophthalmic, oral, or intravaginal use. (2)

3 DOSAGE FORMS AND STRENGTHS

Shampoo, 1%

4 CONTRAINDICATIONS

None

5 WARNINGS AND PRECAUTIONS

- If signs of irritation occur, discontinue use. (5.1)
- Avoid contact with eyes. (5.1)
- Hair discoloration has been reported with ciclopirox use. (5.1)

6 ADVERSE REACTIONS

- The most frequently reported adverse reactions are pruritus, burning, and erythema. (6.1)

To report SUSPECTED ADVERSE REACTIONS, contact Encube Ethicals Private Limited at 1-833-285-4151, and/or FDA at 1-800-FDA-1088 or www.fda.gov/medwatch.

FULL PRESCRIBING INFORMATION

1 INDICATIONS AND USAGE

Ciclopirox shampoo, 1 % is indicated for the topical treatment of seborrheic dermatitis of the scalp in adults.

2 DOSAGE AND ADMINISTRATION

Ciclopirox shampoo is not for ophthalmic, oral, or intravaginal use.

Wet hair and apply approximately 1 teaspoon (5 mL) of ciclopirox shampoo to the scalp. Up to 2 teaspoons (10 ml) may be used for long hair. Lather and leave on hair and scalp for 3 minutes. A timer may be used. Avoid contact with eyes. Rinse off. Treatment should be repeated twice per week for 4 weeks, with a minimum of 3 days between applications.

If a patient with seborrheic dermatitis shows no clinical improvement after 4 weeks of treatment with ciclopirox shampoo, the diagnosis should be reviewed.

3 DOSAGE FORMS AND STRENGTHS

Ciclopirox is a shampoo containing 1 % ciclopirox.

Each gram (equivalent to 0.96 mL) of ciclopirox shampoo contains 10 mg ciclopirox in a colorless and translucent shampoo base.

4 CONTRAINDICATIONS

None.

5 WARNINGS AND PRECAUTIONS

5.1 Local Effects

If a reaction suggesting sensitivity or irritation occurs with the use of ciclopirox shampoo, treatment should be discontinued and appropriate therapy instituted.

Contact of cicloplrox shampoo with the eyes should be avoided. If contact occurs, rinse thoroughly with water.

In patients with lighter hair color, hair discoloration has been reported.

6 ADVERSE REACTIONS

6.1 CLINICAL TRIALS EXPERIENCE

Because clinical trials are conducted under widely varying conditions, adverse reaction rates observed in the clinical trials of a drug cannot be directly compared to rates in the clinical trials of another drug and may not reflect the rates observed in clinical practice.

In 626 subjects treated with ciclopirox shampoo twice weekly in the two pivotal clinical trials, the most frequent adverse events were increased itching in 1% of subjects, and application site reactions, such as burning, erythema, and itching, also in 1 % of subjects.

6.2 POSTMARKETING EXPERIENCE

The following adverse reactions have been identified during post approval use of ciclopirox shampoo: hair discoloration and abnormal hair texture, alopecia, irritation and rash. Because these events are reported voluntarily from a population of uncertain size, it is not possible to reliably estimate their frequency or establish a causal relationship to drug exposure.

8 USE IN SPECIFIC POPULATIONS

8.1 PREGNANCY

Teratogenic Effects: Pregnancy Category B

There are no adequate or well-controlled studies in pregnant women. Therefore, ciclopirox shampoo should be used during pregnancy only if the potential benefit justifies the potential risk to the fetus.

Oral embryofetal developmental studies were conducted in mice, rats, rabbits and monkeys. Ciclopirox or ciclopirox olamine was orally administered during the period of organogenesis. No maternal toxicity, embryotoxicity or teratogenicity were noted at the highest doses of 77, 125, 80 and 38.5 mg/kg/day ciclopirox in mice, rats, rabbits and monkeys, respectively (approximately 13, 42, 54 and 26 times the maximum recommended human dose based on body surface area comparisons, respectively).

Dermal embryofetal developmental studies were conducted in rats and rabbits with ciclopirox olamine dissolved in PEG 400. Ciclopirox olamine was topically administered during the period of organogenesis. No maternal toxicity, embryotoxicity or teratogenicity were noted at the highest doses of 92 mg/kg/day and 77 mg/kg/day ciclopirox in rats and rabbits, respectively (approximately 31 and 54 times the maximum recommended human dose based on body surface area comparisons, respectively).

8.3 NURSING MOTHERS

It is not known whether this drug is excreted in human milk. Because many drugs are excreted in human milk, caution should be exercised when ciclopirox shampoo is administered to a nursing woman.

8.4 PEDIATRIC USE

No clinical trials have been conducted in subjects younger than 16 years.

8.5 GERIATRIC USE

In clinical trials, the safety and tolerability of ciclopirox shampoo in the population 65 years and older was comparable to that of younger subjects. Results of the efficacy analysis in those subjects 65 years and older showed effectiveness in 25 of 85 (29%) subjects treated with ciclopirox shampoo, and in 15 of 61 (25%) subjects treated with the vehicle; due to the small sample size, a statistically significant difference was not demonstrated. Other reported clinical experience has not identified differences in responses between the elderly and younger subjects, but greater sensitivity to adverse effects in some older individuals cannot be ruled out.

11 DESCRIPTION

Ciclopirox shampoo 1 % contains the synthetic antifungal agent, ciclopirox for topical use. Each gram (equivalent to 0.96 ml) of ciclopirox shampoo contains 10 mg ciclopirox m a shampoo base consisting of disodium laureth sulfosuccinate, laureth-2, purified water, sodium chloride, and sodium laureth sulfate.

Ciclopirox shampoo is a colorless, translucent solution. The chemical name for ciclopirox is 6-cyclohexyl-1-hydroxy-4-methyl-2(1H)-pyridone, with the empirical formula C12H17NO2 and a molecular weight of 207.27. The GAS Registry Number is [29342-05-0]. The chemical structure is:

12 CLINICAL PHARMACOLOGY

12.1 MECHANISM OF ACTION

Ciclopirox is a hydroxypyridone antifungal agent although the relevance of this property for the indication of seborrheic dermatitis is not known. Ciclopirox acts by chelation of polyvalent cations (Fe^3+ or Al^3+), resulting in the Inhibition of the metal-dependent enzymes that are responsible for the degradation of peroxides within the fungal cell.

12.2 PHARMACODYNAMICS

The pharmacodynamics of clcloplrox shampoo are unknown.

12.3 PHARMACOKINETICS

In a study in patients with seborrheic dermatitis of the scalp, application of 5 mL ciclopirox shampoo, 1 % twice weekly for 4 weeks, with an exposure time of 3 minutes per application, resulted in detectable serum concentrations of ciclopirox in 6 out of 18 patients. The serum concentrations measured throughout the dosing interval on Days 1 and 29 ranged from 10.3 ng/mL to 13.2 ng/ml. Total urinary excretion of ciclopirox was less than 0.5% of the administered dose.

12.4 MICROBIOLOGY

Ciclopirox is fungicidalin vitro against Malassezia furfur (Pityrosporum spp.), P. ovale, and P. orbiculare.

The clinical significance of antifungal activity in the treatment of seborrheic dermatitis is not known.

13 NONCLINICAL TOXICOLOGY

13.1 CARCINOGENESIS & MUTAGENESIS & IMPAIRMENT OF FERTILITY

A 104-week dermal carcinogenicity study in mice was conducted with ciclopirox cream applied at doses up to 1.93% (100 mg/kg/day or 300 mglm2/day). No increase in drug related neoplasms was noted when compared to control.

The following In vitro genotoxicity tests have been conducted with ciclopirox: evaluation of gene mutation in the Ames Salmonella and E. coli assays (negative); chromosome aberration assays in V79 Chinese hamster lung fibroblast cells, with and without metabolic activation (positive); chromosome aberration assays in V79 Chinese hamster lung fibroblast cells in the presence of supplemental Fe3+, with and without metabolic activation (negative); gene mutation assays in the HGPRT-test with V79 Chinese hamster lung fibroblast cells (negative); and a primary DNA damage assay (i.e., unscheduled DNA synthesis assay in A549 human cells) (negative). An in vitro cell transformation assay in BALB/c 3T3 cells was negative for cell transformation. In an in vivo Chinese hamster bone marrow cytogenetic assay, ciclopirox was negative for chromosome aberrations at a dosage of 5,000 mg/kg body weight.

A combined oral fertility and embryofetal developmental study was conducted in rats with ciclopirox olamine. No effect on fertility or reproductive performance was noted at the highest dose tested of 3.85 mg/kg/day ciclopirox (approximately 1.3 times the maximum recommended human dose based on body surface area comparisons).

14 CLINICAL STUDIES

In two randomized, double-blind clinical trials, subjects 16 years and older with seborrheic dermatitis of the scalp applied ciclopirox shampoo or its vehicle twice weekly for 4 weeks. Subjects who were immune- compromised, those with psoriasis or atopic dermatitis, women of childbearing potential not using adequate contraception, and pregnant or lactating women were excluded from the clinical trials. An evaluation of the overall status of the seborrheic dermatitis, the presence and severity of erythema or inflammation, and scaling, was made at Week 4, using a scale of 0 = none, 1 = slight, 2 = mild, 3 = moderate, 4 = pronounced, and 5 = severe. Effective treatment was defined as achieving a score of o (or a score of 1 If the baseline score was ≥ 3) simultaneously for status of the seborrheic dermatitis, erythema or inflammation, and scaling at Week 4.

Ciclopirox shampoo was shown to be statistically significantly more effective than vehicle in both trials. Efficacy results for the two trials are presented in Table 1 below.

Table 1. Effective Treatment Rates at Week 4 in Trials 1 and 2

 | Clcloplrox Shampoo | Vehicle
Study 1 | 220/380 (58%) | 60/192 (31%)
Study 2 | 65/250 (26%) | 32/249 (1 3%)

Efficacy for African American subjects was not demonstrated, although only 53African American subjects were enrolled in the two pivotal trials.

16 HOW SUPPLIED

Ciclopirox shampoo, 1 % is colorless and translucent, and supplied in 120 mL plastic bottles (NOC 21922-105-52).

Discard unused product after initial treatment duration. Store between 15°C and 30°C (59° F and 86° F).

Keep out of reach of children.

17 PATIENT COUNSELING INFORMATION

Advise the patient to read the FDA-approved patient labeling (Patient Information).

The patient should be instructed to:

- Use cicloplrox shampoo as directed by the physician. Avoid contact with the eyes. If contact occurs, rinse thoroughly with water. Ciclopirox shampoo is for external use on the scalp only. Do not swallow.
- Use ciclopirox shampoo for seborrheic dermatitis for the full treatment time even though symptoms may have improved. Notify the physician if there is no improvement after 4 weeks.
- Inform the physician if the area of application shows signs of increased initation (redness, itching, burning, blistering, swelling, or oozing).

Manufactured by:

Encube Ethicals Pvt. Ltd.

Plot No. C-1, Madkaim

Industrial Estate, Madkaim,

Post: Mardol, Panda,

Goa - 403 404, India.

Distributed by:

Encube Ethicals, Inc.

200 Meredith Drive,

Suite 202, Durham,

NC27713 USA

Revision: 05/2025

PATIENT INFORMATION

Ciclopirox (sye" kloe pir' ox) Shampoo

Important: For use on the scalp only. Do not get ciclopirox shampoo in your eyes, mouth, or vagina.

What is ciclopirox shampoo?

Ciclopirox shampoo is a prescription medicine used on the scalp to treat adults with a skin condition called seborrheic dermatitis.

It is not known if ciclopirox shampoo is safe and effective in children under 16 years of age.

What should I tell my doctor before using ciclopirox shampoo?

Before using ciclopirox shampoo, tell your doctor if you:

- have any other medical conditions
- are pregnant or plan to become pregnant. It is not known if ciclopirox shampoo will harm your unborn baby.
- are breastfeeding or plan to breastfeed. It is not known if ciclopirox shampoo passes into your breast milk.
- are taking prescription and nonprescription medicines, vitamins, and herbal supplements.

Know the medicines you take. Keep a list of them to show your doctor and pharmacist when you get a new medicine.

How should I use ciclopirox shampoo?

- Use ciclopirox shampoo exactly as your doctor tells you to use it.
- Wash your hair using ciclopirox shampoo 2 times each week for 4 weeks. There should be at least 3 days between each time you use ciclopirox shampoo.
- Use ciclopirox shampoo for 4 weeks even if your skin condition improves.
- Tell your doctor if your scalp condition is not getting better after you have used ciclopirox shampoo for 4 weeks.
- Do not swallow ciclopirox shampoo.
- Avoid getting ciclopirox shampoo in your eyes. If ciclopirox shampoo gets into your eyes, rinse them well with water.

How should I apply ciclopirox shampoo?

- Wet your hair and apply approximately 1 teaspoon of ciclopirox shampoo to your scalp. You may use up to 2 teaspoons of ciclopirox shampoo if you have long hair. Lather and leave ciclopirox shampoo on your hair and scalp for 3 minutes. You may use a timer.
- After 3 minutes have passed, rinse your hair and scalp.

What are the possible side effects of ciclopirox shampoo?

The most common side effects of ciclopirox shampoo include: itching, burning, and redness of the scalp. Tell your doctor if you get any of these symptoms and they become worse or do not go away, or if you get blistering, swelling, or oozing in your scalp.

These are not all the possible side effects of ciclopirox shampoo. For more information, ask your doctor.

Call your doctor for medical advice about side effects. You may report side effects to FDA at 1-800-FDA-1088.

How should I store ciclopirox shampoo?

- Store ciclopirox shampoo at room temperature, between 59°F to 86°F (15°Cto30°C).
- Safely throw away any unused ciclopirox shampoo after you finish your treatment.

Keep ciclopirox shampoo and all medicines out of the reach of children.

General information about ciclopirox shampoo

Medicines are sometimes prescribed for purposes other than those listed in a Patient Information leaflet. Do not use ciclopirox shampoo for a condition for which it was not prescribed. Do not give ciclopirox shampoo to other people, even if they have the same symptoms you have. It may harm them.

You can ask your pharmacist or doctor for information about ciclopirox shampoo that is written for health professionals.

For more information about ciclopirox shampoo, call 1-833-285-4151.

What are the ingredients in ciclopirox shampoo?

Active ingredient: ciclopirox

Inactive ingredients: disodium laureth sulfosuccinate, laureth-2, purified water, sodium chloride, and sodium laureth sulfate.

This Patient Information has been approved by the U.S. Food and Drug Administration.

Manufactured by:

Encube Ethicals Pvt. Ltd.

PlotNo. C-1, Madkaim

Industrial Estate, Madkaim,

Post: Mardol, Panda,

Goa - 403 404, India.

Distributed by:

Encube Ethicals, Inc.

200 Meredith Drive,

Suite 202, Durham,

NC 27713 USA

Revision: 05/2025

PACKAGE LABEL.PRINCIPAL DISPLAY PANEL

NDC 21922-105-52

Ciclopirox Shampoo 1%

For Topical Use Only

Not for Ophthalmic,

Oral or Intravaginal Use.

Keep Out of Reach of Children

RX only

120 mL